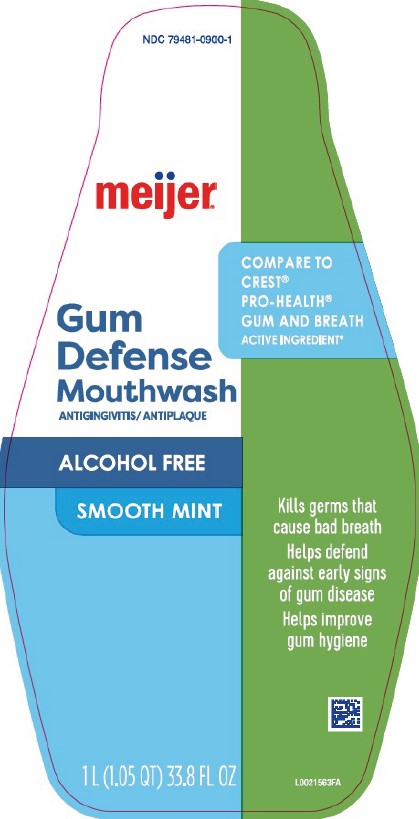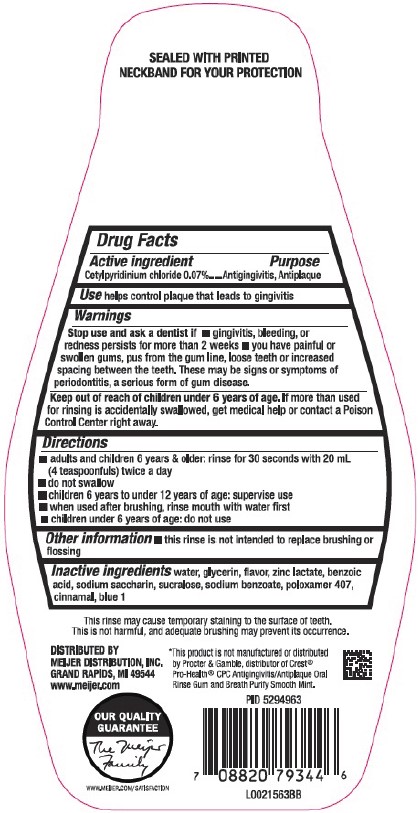 DRUG LABEL: Antigingivitis/Antiplaque
NDC: 79481-0900 | Form: MOUTHWASH
Manufacturer: Meijer, Inc.
Category: otc | Type: HUMAN OTC DRUG LABEL
Date: 20260224

ACTIVE INGREDIENTS: CETYLPYRIDINIUM CHLORIDE 0.7 mg/1 mL
INACTIVE INGREDIENTS: WATER; GLYCERIN; ZINC LACTATE; BENZOIC ACID; SACCHARIN SODIUM; SUCRALOSE; SODIUM BENZOATE; POLOXAMER 407; CINNAMALDEHYDE; FD&C BLUE NO. 1

Meijer D00.001/D00AA
Alcohol-Free Gum Defense Mouthwash

Tamper Evident Statement

SEALED WITH PRINTED NECKBAND FOR YOUR PROTECTION

Active Ingredient

Cetylpyridinium Chloride 0.07%

Purpose

Antigingivitis, Antiplaque

Use

helps control plaque that leads to gingivitis

Warnings

For this product

Stop use and ask a dentist if

- gingivitis, bleeding, or redness persists for more than 2 weeks
- you have painful or swollen gums, pus from the gum line, loose teeth or increased spacing between the teeth. These may be signs or symptoms of periodontitis, a serious form of gum disease.

Keep out of reach of children under 6 years of age.

If more than used for rinsing is accidentally swallowed, get medical help or contact a Poison Control Center right away.

Directions

- adults and children 6 years & older: rinse for 30 seconds with 20 mL (4 teaspoonfuls) twice a day
- do not swallow
- children 6 years to under 12 years of age: supervise use
- when used after brushing, rinse mouth with water first
- children under 6 years of age: do not use

Other information

- this rinse is not intended to replace brushing or flossing

Inactive ingredients

water, glycerin, flavor, zinc lactate, benzoic acid, sodium saccharin, sucralose, sodium benzoate, poloxamer 407, cinnamal, blue 1

Disclaimers

This may cause temporary staining to the surface of teeth. This is not harmful, and adequate brushing may prevent its occurrence.

*This product is not manufactured or distributed by Procter & Gamble, distributor of Crest® Pro-Health® CPC Antiginigivitis/Antiplaque Oral Rinse Gum and Breath Purify Smooth Mint.

ADVERSE REACTION

DISTRIBUTED BY

MEIJER DISTRIBUTION, INC.

GRAND RAPIDS, MI 49544

www.meijer.com

OUR QUALITY GUARANTEE

The Meijer Family

WWW.MEIJER.COM/SATISFACTION

Principal Display Panel

NDC 79481-0900-1

meijer®

COMPARE TO CREST®PRO-HEALTH® GUM AND BREATH ACTIVE INGREDIENT*

Gum Defense Mouthwash

ANTIGINGIVITIS/ANTIPLAQUE

ALCOHOL FREE

SMOOTH MINT

Kills germs that cause bad breath

Helps defend against early signs of gum disease

Helps improve gum hygiene

1 L (1.5 QT) 33.8 FL OZ